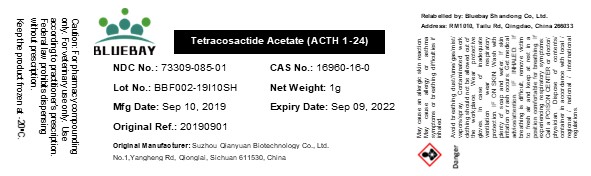 DRUG LABEL: Tetracosactide Acetate (ACTH 1-24)
NDC: 73309-085 | Form: POWDER
Manufacturer: BLUEBAY SHANDONG CO.,LTD
Category: other | Type: BULK INGREDIENT
Date: 20200117

ACTIVE INGREDIENTS: COSYNTROPIN 1 g/1 g

Tetracosactide Acetate (ACTH 1-24)